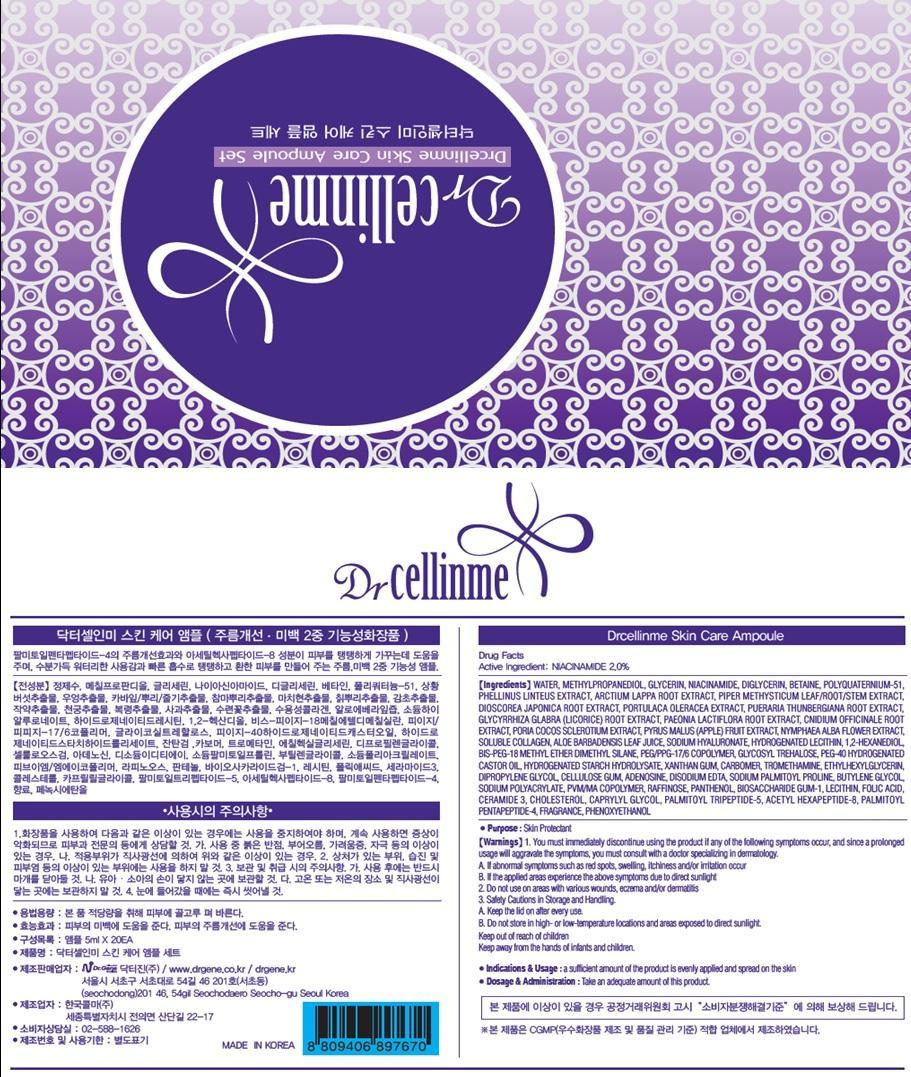 DRUG LABEL: Dr Cellinme Skin Care Ampoule
NDC: 69783-030 | Form: SOLUTION
Manufacturer: Dr.Gene Co.,Ltd
Category: otc | Type: HUMAN OTC DRUG LABEL
Date: 20150728

ACTIVE INGREDIENTS: Niacinamide 0.1 mg/20 1
INACTIVE INGREDIENTS: WATER; METHYLPROPANEDIOL

ACTIVE INGREDIENT

Active Ingredient: Niacinamide 2.0%

INACTIVE INGREDIENT

Inactive Ingredients: WATER, METHYLPROPANEDIOL, GLYCERIN, BETAINE, DIGLYCERIN, POLYQUATERNIUM-51, PIPER METHYSTICUM LEAF/ROOT/STEM EXTRACT, ALOE BARBADENSIS LEAF JUICE, 1,2-HEXANEDIOL, ARCTIUM LAPPA ROOT EXTRACT, PHELLINUS LINTEUS EXTRACT, SOLUBLE COLLAGEN, HYDROGENATED LECITHIN, GLYCOSYL TREHALOSE, PHENOXYETHANOL, HYDROGENATED STARCH HYDROLYSATE, XANTHAN GUM, DIOSCOREA JAPONICA ROOT EXTRACT, PORTULACA OLERACEA EXTRACT, PUERARIA THUNBERGIANA ROOT EXTRACT, CNIDIUM OFFICINALE ROOT EXTRACT, GLYCYRRHIZA GLABRA (LICORICE) ROOT EXTRACT, PAEONIA LACTIFLORA ROOT EXTRACT, TROMETHAMINE, ETHYLHEXYLGLYCERIN, PORIA COCOS SCLEROTIUM EXTRACT, PYRUS MALUS (APPLE) FRUIT EXTRACT, NYMPHAEA ALBA FLOWER EXTRACT, DIPROPYLENE GLYCOL, CELLULOSE GUM, ADENOSINE, DISODIUM EDTA, FRAGRANCE, SODIUM HYALURONATE, SODIUM PALMITOYL PROLINE, BUTYLENE GLYCOL, BIS-PEG-18 METHYL ETHER DIMETHYL SILANE, PEG/PPG-17/6 COPOLYMER, PEG-40 HYDROGENATED CASTOR OIL, CARBOMER, PVM/MA COPOLYMER, SODIUM POLYACRYLATE, RAFFINOSE, BIOSACCHARIDE GUM-1, LECITHIN, FOLIC ACID, CERAMIDE 3, CHOLESTEROL, CAPRYLYL GLYCOL, PANTHENOL, PALMITOYL TRIPEPTIDE-5, ACETYL HEXAPEPTIDE-8, PALMITOYL PENTAPEPTIDE-4

PURPOSE

Purpose: Skin Protectant

WARNINGS

Warnings: 1. You must immediately discontinue using the product if any of the following symptoms occur, and since a prolonged usage will aggressive the symptoms, you must consult with a doctor specializing in dermatology. A. If abnormal symptoms such as red spots, swelling, itchiness and/or irritation occur. B. If the applied experience the above symptoms due to direct sunlight. 2. Do not use on areas with various wounds, eczema and/or dermatitis those who are sensitive to adhesive band-aids or poultice must take caution when using it. Keep away from your eyes and be sure to clean it immediately if it ever gets into an eye. 3. Safety cautions in storage and handling. A. Use immediately after you open the product. B. Do not store in high or low temperature locations and areas exposed to direct sunlight. C. Do not reuse a product that has already been used before. Keep out of reach of children. Keep away from the hands of infants and children.

Keep out of reach of children. Keep away from the hands of infants and children.

INDICATIONS & USAGE

Indications & usage: A sufficient amount of the product is evenly applied and spread on the skin.

DOSAGE & ADMINISTRATION

Dosage & Administration: Take an appropriate amount of this product.